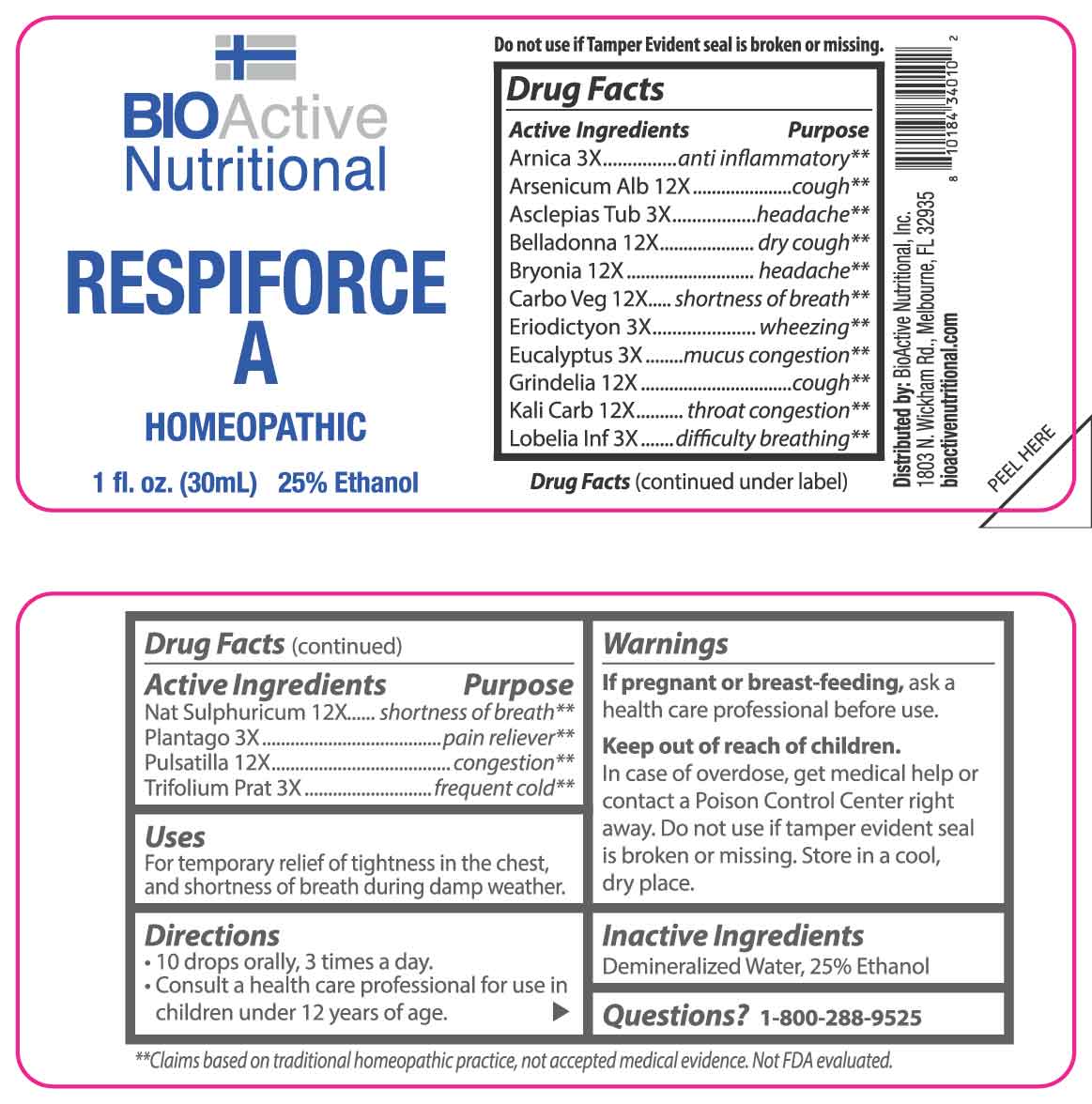 DRUG LABEL: Respiforce A
NDC: 43857-0599 | Form: LIQUID
Manufacturer: BioActive Nutritional
Category: homeopathic | Type: HUMAN OTC DRUG LABEL
Date: 20250402

ACTIVE INGREDIENTS: ARNICA MONTANA WHOLE 3 [hp_X]/1 mL; ASCLEPIAS TUBEROSA ROOT 3 [hp_X]/1 mL; ERIODICTYON CALIFORNICUM LEAF 3 [hp_X]/1 mL; EUCALYPTUS GLOBULUS LEAF 3 [hp_X]/1 mL; LOBELIA INFLATA WHOLE 3 [hp_X]/1 mL; PLANTAGO MAJOR WHOLE 3 [hp_X]/1 mL; TRIFOLIUM PRATENSE FLOWER 3 [hp_X]/1 mL; ARSENIC TRIOXIDE 12 [hp_X]/1 mL; ATROPA BELLADONNA 12 [hp_X]/1 mL; BRYONIA ALBA ROOT 12 [hp_X]/1 mL; ACTIVATED CHARCOAL 12 [hp_X]/1 mL; GRINDELIA HIRSUTULA FLOWERING TOP 12 [hp_X]/1 mL; POTASSIUM CARBONATE 12 [hp_X]/1 mL; SODIUM SULFATE 12 [hp_X]/1 mL; PULSATILLA VULGARIS WHOLE 12 [hp_X]/1 mL
INACTIVE INGREDIENTS: WATER; ALCOHOL

DRUG FACTS:

ACTIVE INGREDIENTS:

Arnica Montana 3X, Arsenicum Album 12X, Asclepias Tuberosa 3X, Belladonna 12X, Bryonia 12X, Carbo Vegetabilis 12X, Eriodictyon Californicum 3X, Eucalyptus Globulus 3X, Grindelia 12X, Kali Carbonicum 12X, Lobelia Inflata 3X, Natrum Sulphuricum 12X, Plantago Major 3X, Pulsatilla 12X, Trifolium Pratense 3X.

PURPOSE:

Arnica Montana – anti inflammatory,** Arsenicum Album - cough,** Asclepias Tuberosa - headache,** Belladonna – dry cough,** Bryonia - headache,** Carbo Vegetabilis – shortness of breath,** Eriodictyon Californicum - wheezing,** Eucalyptus Globulus – mucus congestion,** Grindelia - cough,** Kali Carbonicum – throat congestion,** Lobelia Inflata – difficulty breathing,** Natrum Sulphuricum – shortness of breath,** Plantago Major – pain reliever,** Pulsatilla - congestion,** Trifolium Pratense – frequent cold**

**Claims based on traditional homeopathic practice, not accepted medical evidence. Not FDA evaluated.

USES:

For temporary relief of tightness in the chest, and shortness of breath during damp weather.

WARNINGS:

If pregnant or breast-feeding, ask a health care professional before use.

Keep out of reach of children. In case of overdose, get medical help or contact a Poison Control Center right away.

Do not use if tamper evident seal is broken or missing.

Store in a cool, dry place.

KEEP OUT OF REACH OF CHILDREN:

In case of overdose, get medical help or contact a Poison Control Center right away.

DIRECTIONS:

• 10 drops orally, 3 times a day.

• Consult a health care professional for use in children under 12 years of age.

INACTIVE INGREDIENTS:

Demineralized Water, 25% Ethanol

QUESTIONS:

Distributed by:
BioActive Nutritional, Inc.
1803 N. Wickham Rd.
Melbourne, FL 32935
bioactivenutritional.com

1-800-288-9525

PACKAGE LABEL DISPLAY:

BIOActive Nutritional

RESPIFORCE A

HOMEOPATHIC

1 FL OZ (30 ml)